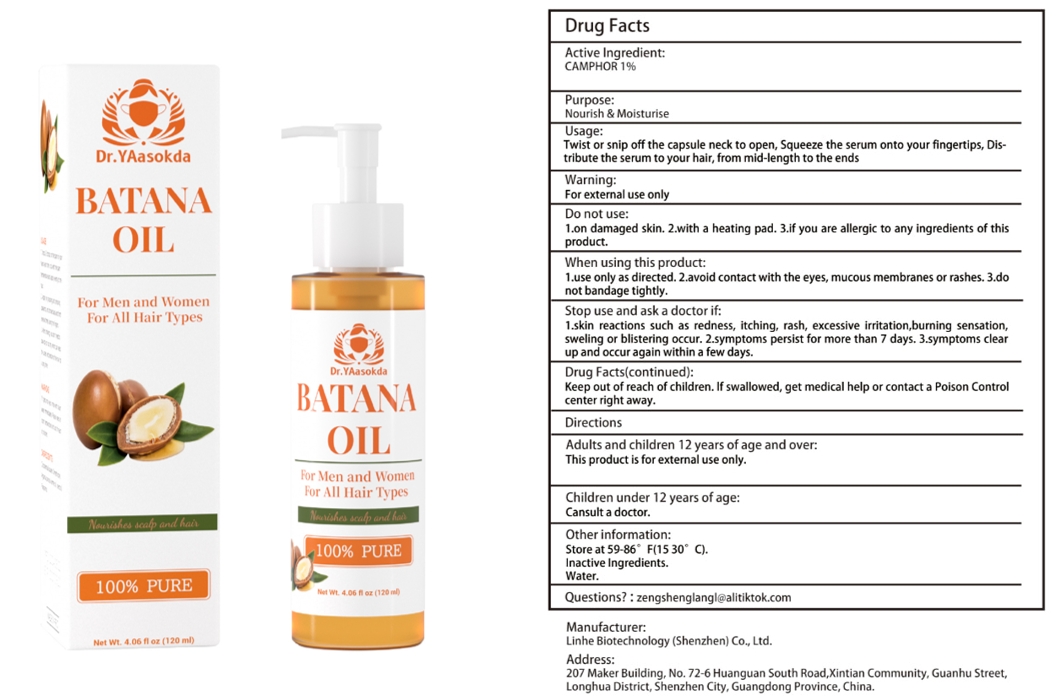 DRUG LABEL: Batana oil
NDC: 84575-043 | Form: LIQUID
Manufacturer: Linhe Biotechnology (Shenzhen) Co., Ltd
Category: otc | Type: HUMAN OTC DRUG LABEL
Date: 20241109

ACTIVE INGREDIENTS: CAMPHOR, (-)- 0.12 g/120 mL
INACTIVE INGREDIENTS: GLYCERIN

Batana Oil

ACTIVE INGREDIENT

CAMPHOR 1%

PURPOSE

Nourish & Moisturise

INDICATIONS AND USAGE

Twist or snip off the capsule neck to open, Squeeze the serum onto your fingertips, Distribute the serum to your hair, from mid-length to the ends

WARNINGS

Twist or snip off the capsule neck to open, Squeeze the serum onto your fingertips, Distribute the serum to your hair, from mid-length to the ends

DOSAGE AND ADMINISTRATION

Take this product and spray it on the glans and coronal sulcus. Spray 1-2 times each time to avoid the urethral opening.

INACTIVE INGREDIENT

WATER

STORAGE AND HANDLING

Store in a cool and dark place away from light

Keep out of reach of children,in case of overdose, get medical help or contact a PoisonControl Center right away.